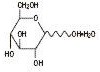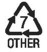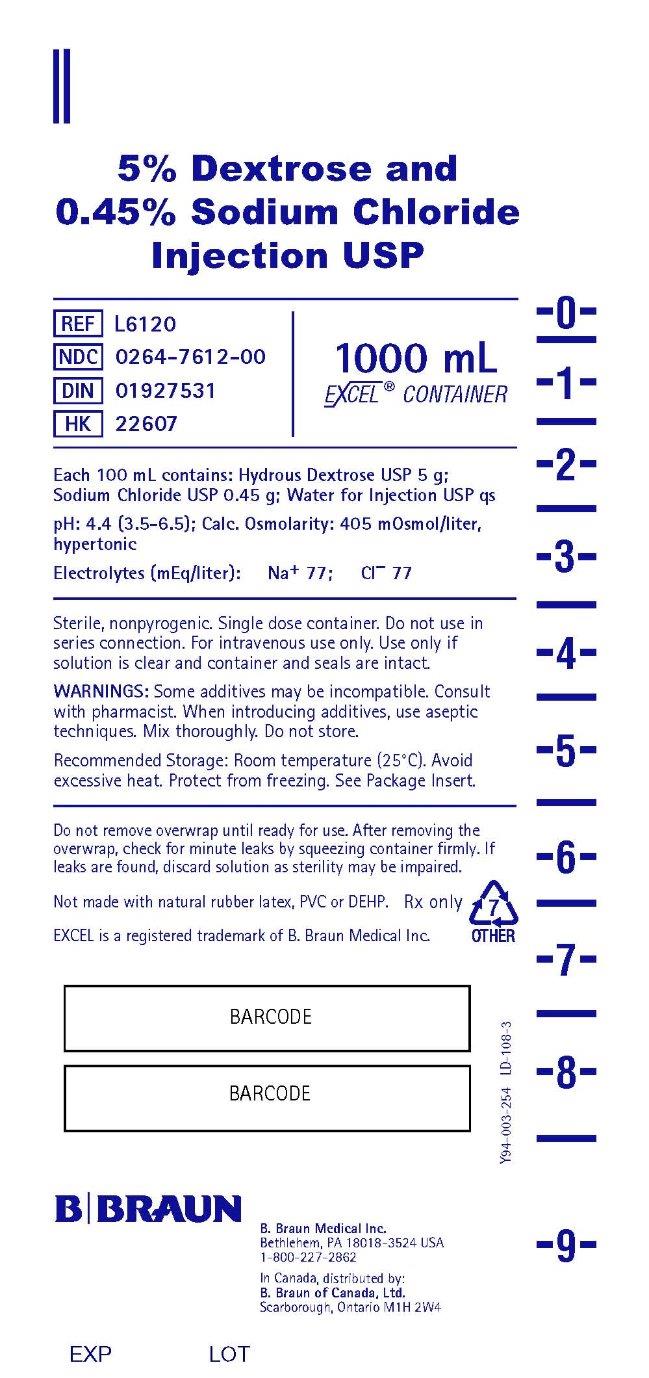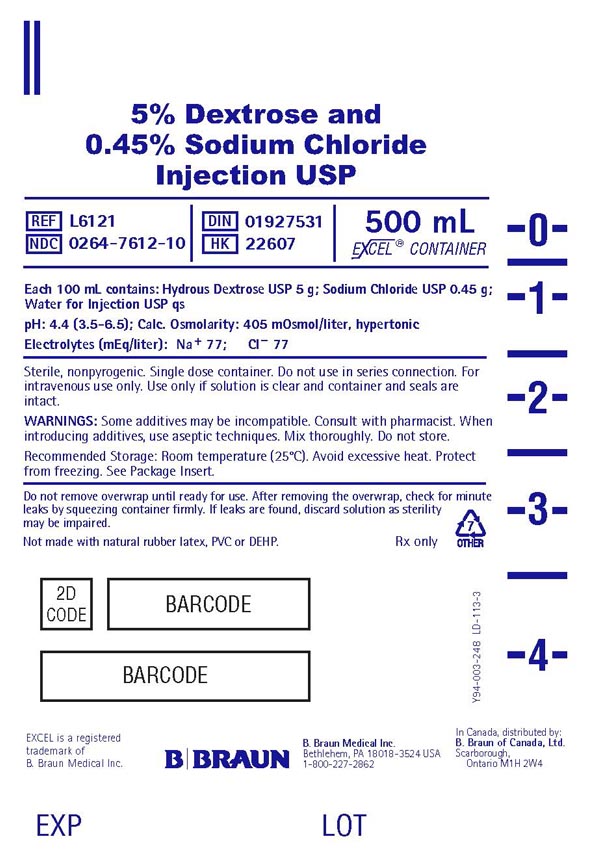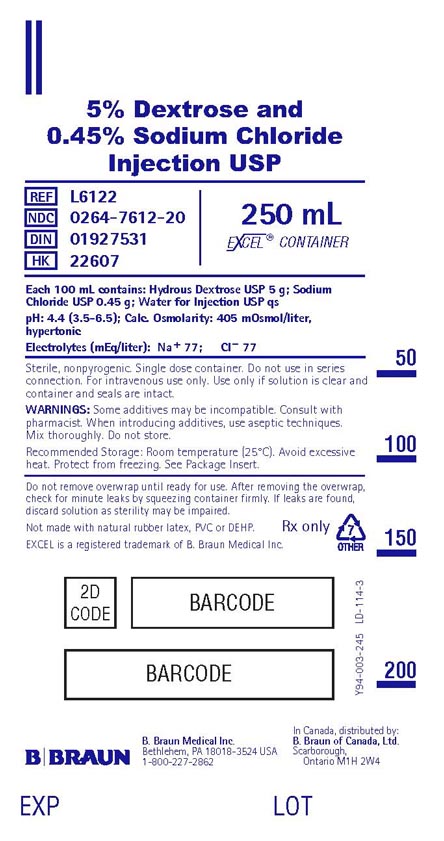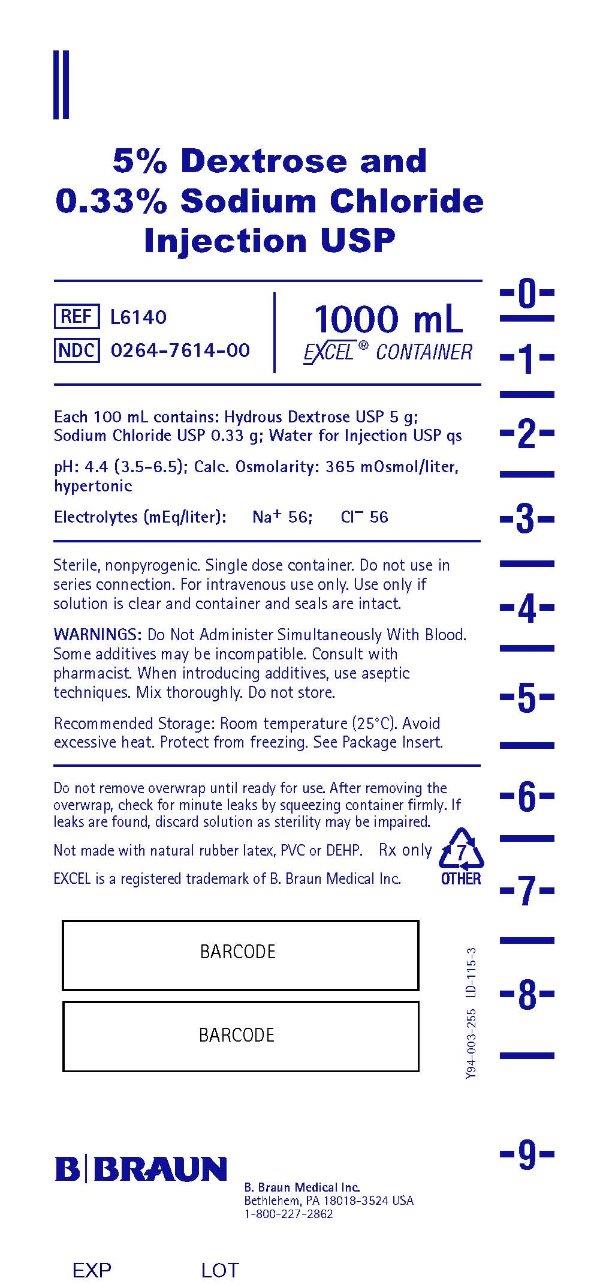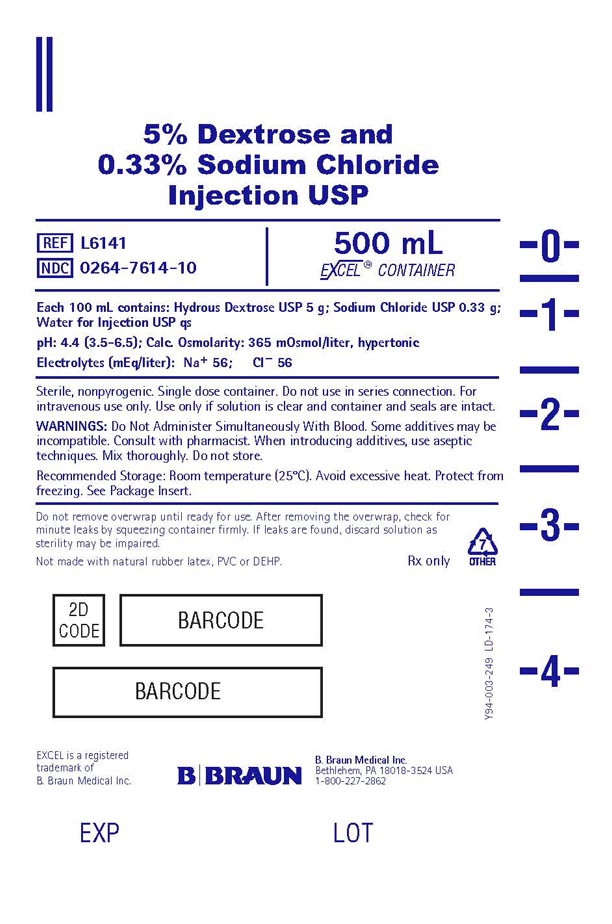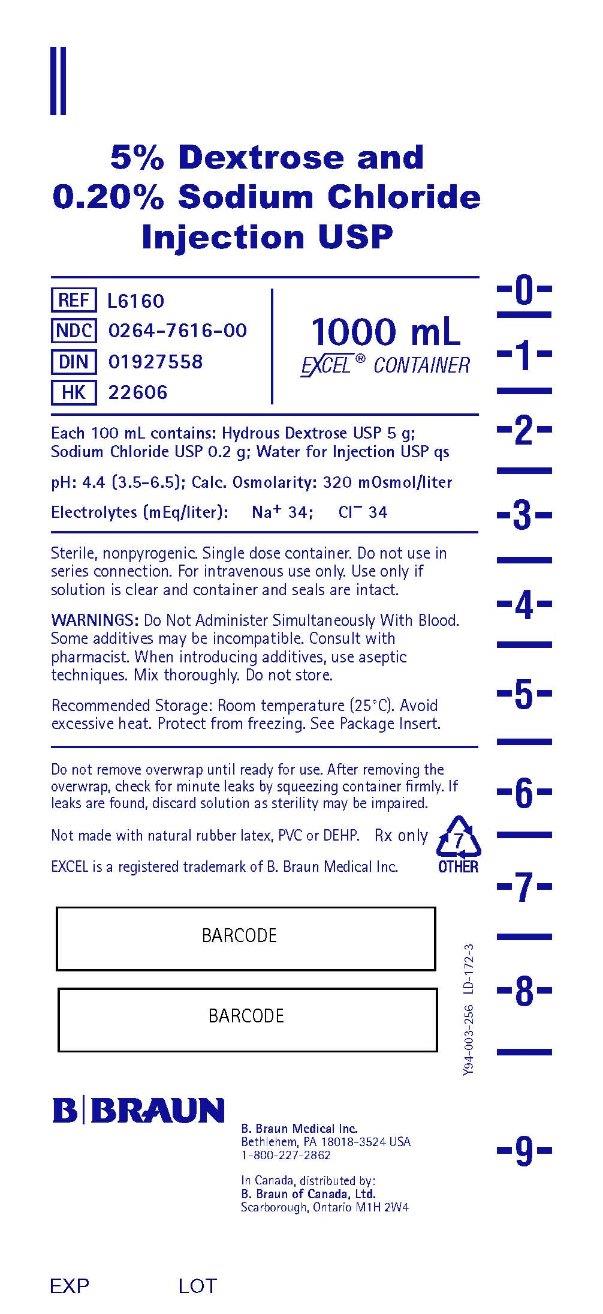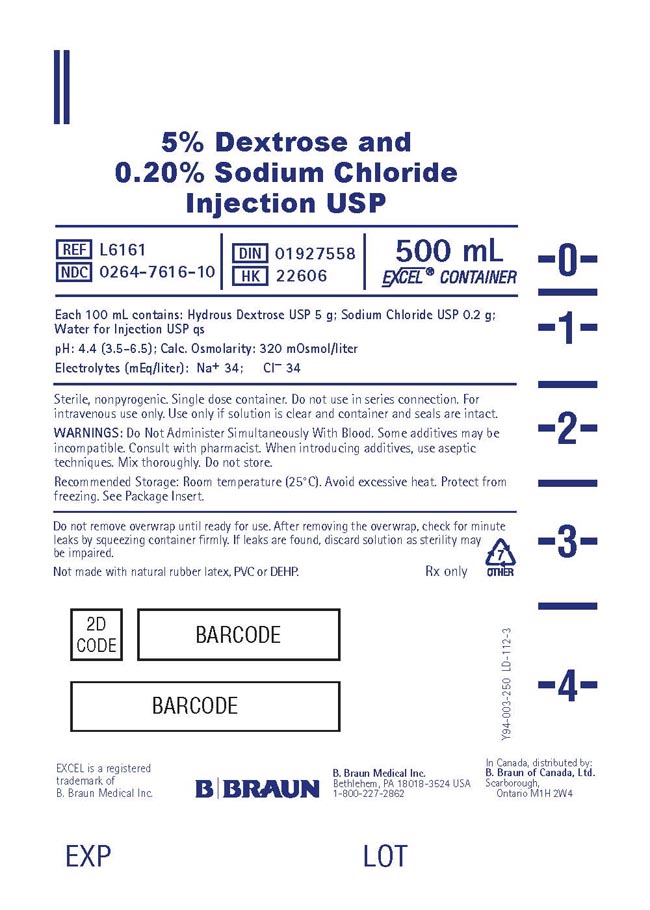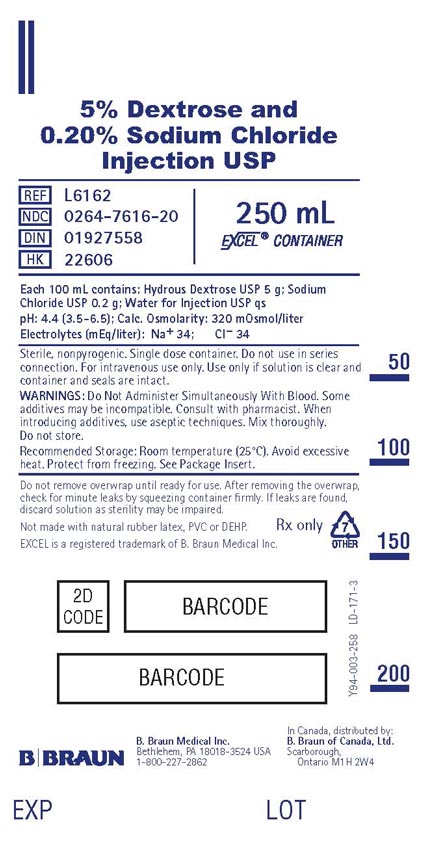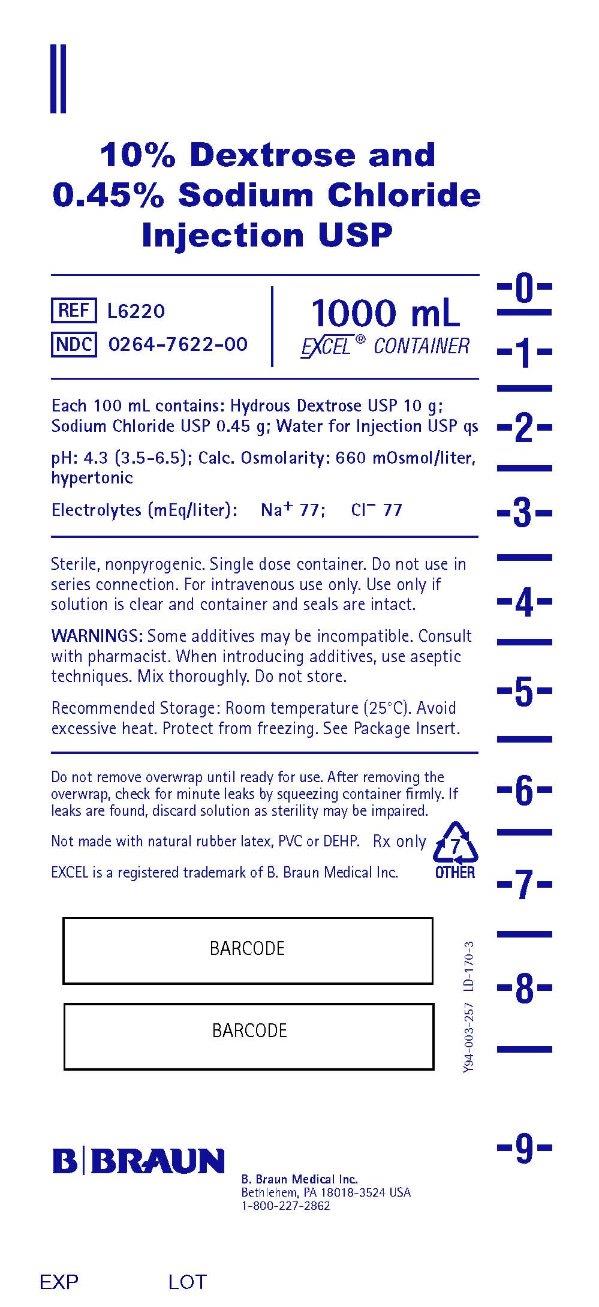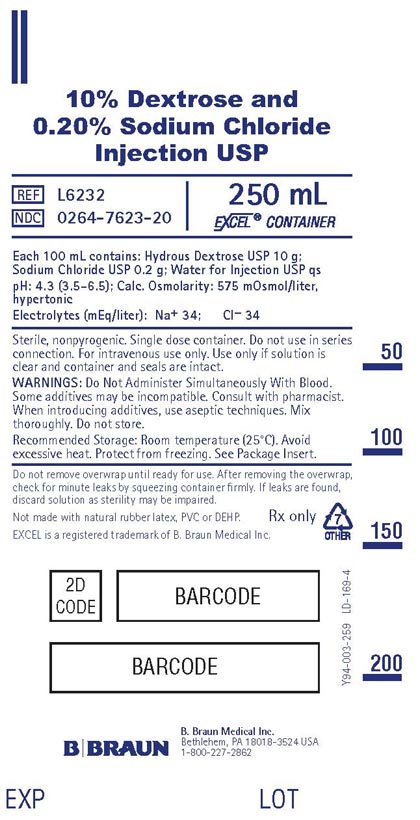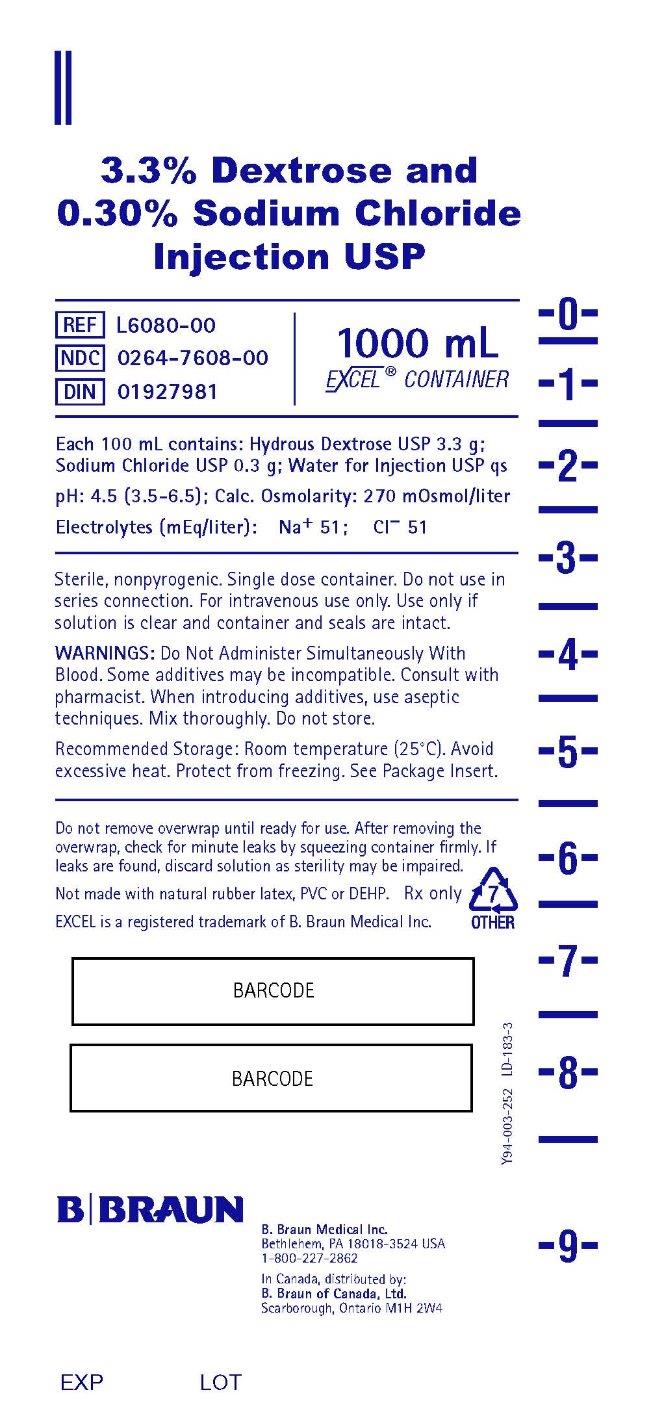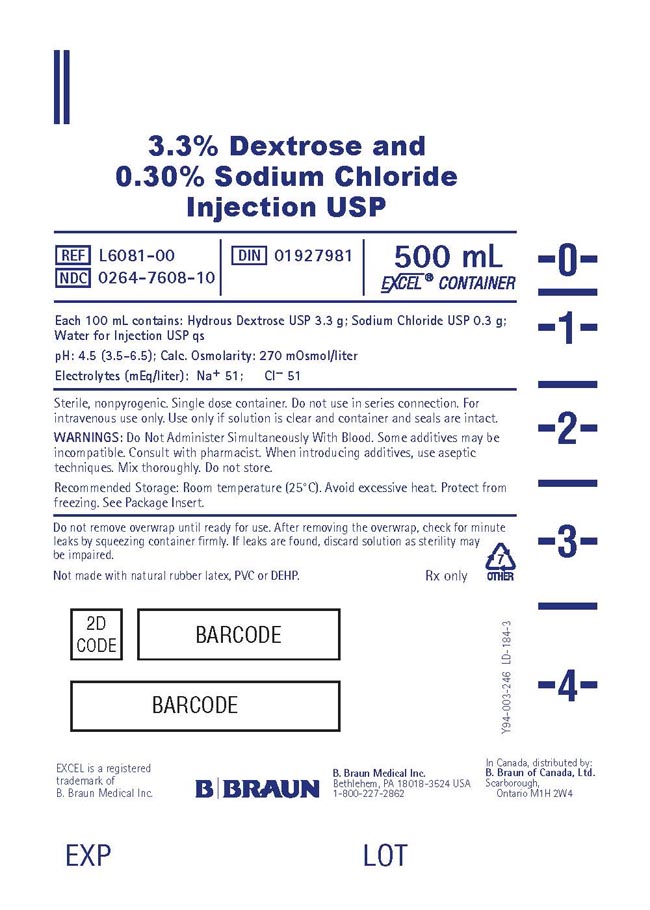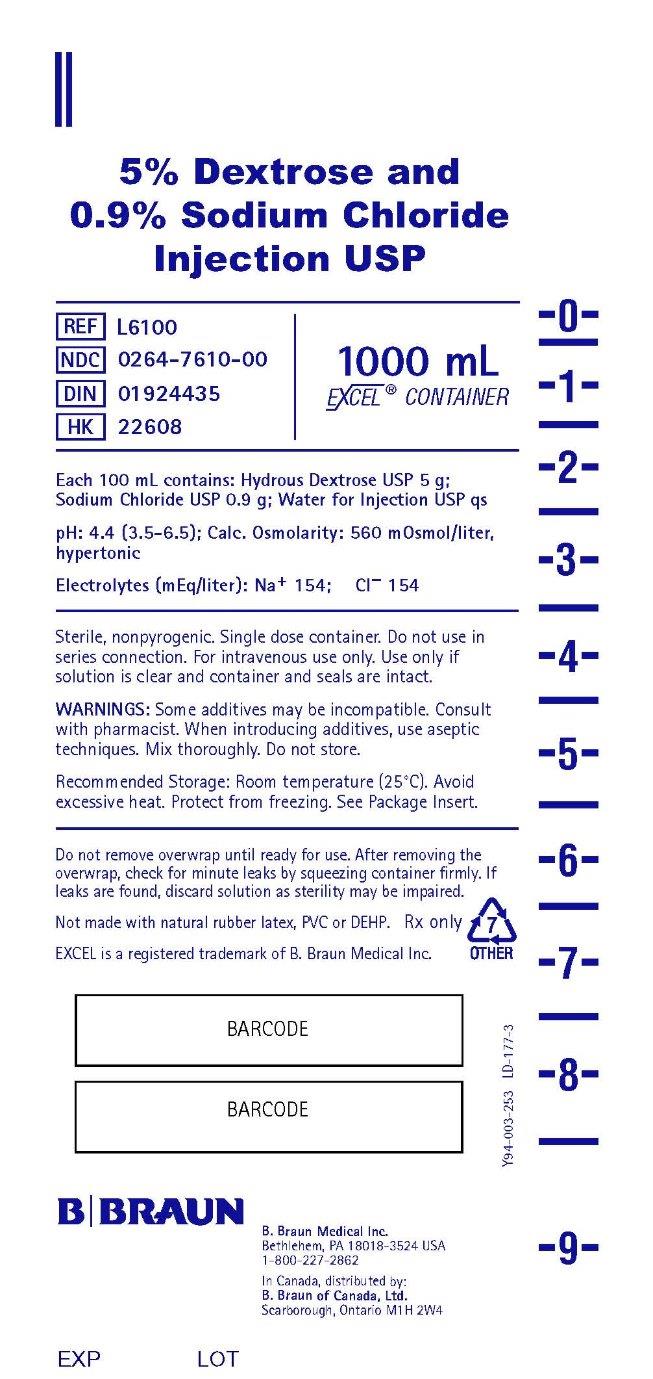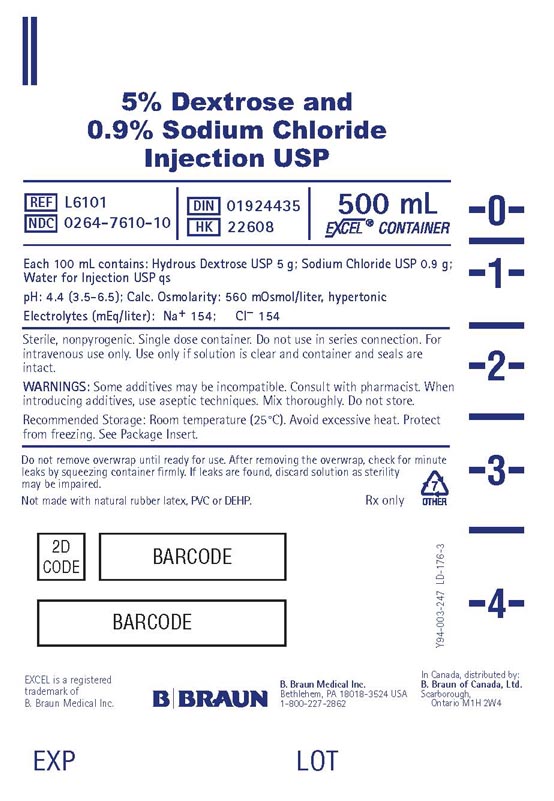 DRUG LABEL: Dextrose And Sodium Chloride
NDC: 0264-7605 | Form: INJECTION, SOLUTION
Manufacturer: B. Braun Medical Inc.
Category: prescription | Type: HUMAN PRESCRIPTION DRUG LABEL
Date: 20240402

ACTIVE INGREDIENTS: DEXTROSE, UNSPECIFIED FORM 2.5 g/100 mL; SODIUM CHLORIDE 0.45 g/100 mL
INACTIVE INGREDIENTS: WATER

Dextrose and
Sodium Chloride Injections USP

DESCRIPTION

(See chart below for quantitative information.)

Dextrose and Sodium Chloride Injections USP are sterile, nonpyrogenic and contain no bacteriostatic or antimicrobial agents. These products are intended for intravenous administration.

The formulas of the active ingredients are:

Ingredients | Molecular Formula | Molecular Weight
Sodium Chloride USP | NaCl | 58.44
Hydrous Dextrose USP |  | 198.17

Composition – Each 100 mL contains: |  |  | Concentration of Electrolytes (mEq/liter)
 | Hydrous Dextrose USP | Sodium Chloride USP | Concentration of Electrolytes (mEq/liter) |  | Calories per liter | Calculated Osmolarity mOsmol/liter | pH
Solution | Hydrous Dextrose USP | Sodium Chloride USP | Sodium | Chloride | Calories per liter | Calculated Osmolarity mOsmol/liter | pH
Solution | 3.3% Dextrose and 0.30% Sodium Chloride Injection USP | 3.3 g | Sodium | Chloride | 0.3 g | 51 | 51 | 110 | 270 | 4.5 (3.5–6.5)
5% Dextrose and 0.9% Sodium Chloride Injection USP | 5 g | 0.9 g | 154 | 154 | 170 | 560 | 4.4 (3.5–6.5)
5% Dextrose and 0.45% Sodium Chloride Injection USP | 5 g | 0.45 g | 77 | 77 | 170 | 405 | 4.4 (3.5–6.5)
5% Dextrose and 0.33% Sodium Chloride Injection USP | 5 g | 0.33 g | 56 | 56 | 170 | 365 | 4.4 (3.5–6.5)
5% Dextrose and 0.20% Sodium Chloride Injection USP | 5 g | 0.2 g | 34 | 34 | 170 | 320 | 4.4 (3.5–6.5)
10% Dextrose and 0.45% Sodium Chloride Injection USP | 10 g | 0.45 g | 77 | 77 | 340 | 660 | 4.3 (3.5–6.5)
10% Dextrose and 0.20% Sodium Chloride Injection USP | 10 g | 0.2 g | 34 | 34 | 340 | 575 | 4.3 (3.5–6.5)
Water for Injection USP qs

Not made with natural rubber latex, PVC or DEHP.

The plastic container is made from a multilayered film specifically developed for parenteral drugs. It contains no plasticizers and exhibits virtually no leachables. The solution contact layer is a rubberized copolymer of ethylene and propylene. The container is nontoxic and biologically inert. The container-solution unit is a closed system and is not dependent upon entry of external air during administration. The container is overwrapped to provide protection from the physical environment and to provide an additional moisture barrier when necessary.

Addition of medication should be accomplished using complete aseptic technique.

The closure system has two ports; the one for the administration set has a tamper evident plastic protector and the other is a medication addition site. Refer to the Directions for Use of the container.

CLINICAL PHARMACOLOGY

Dextrose and Sodium Chloride Injections USP provide electrolytes and calories and are a source of water for hydration. All are capable of inducing diuresis depending on the clinical condition of the patient.

Sodium, the major cation of the extracellular fluid, functions primarily in the control of water distribution, fluid balance, and osmotic pressure of body fluids. Sodium is also associated with chloride and bicarbonate in the regulation of the acid-base equilibrium of body fluid.

Chloride, the major extracellular anion, closely follows the metabolism of sodium, and changes in the acid-base balance of the body are reflected by changes in the chloride concentration.

Dextrose provides a source of calories. Dextrose is readily metabolized, may decrease losses of body protein and nitrogen, promotes glycogen deposition and decreases or prevents ketosis if sufficient doses are provided.

INDICATIONS AND USAGE

These intravenous solutions are indicated for use in adults and pediatric patients as sources of electrolytes, calories and water for hydration.

CONTRAINDICATIONS

These solutions are contraindicated where the administration of sodium or chloride could be clinically detrimental.

Solutions containing dextrose may be contraindicated in patients with hypersensitivity to corn products.

WARNINGS

The administration of intravenous solutions can cause fluid and/or solute overload resulting in dilution of serum electrolyte concentrations, overhydration, congested states or pulmonary edema. The risk of dilutional states is inversely proportional to the electrolyte concentration. The risk of solute overload causing congested states with peripheral and pulmonary edema is directly proportional to the electrolyte concentration. Solutions containing sodium ions should be used with great care, if at all, in patients with congestive heart failure, severe renal insufficiency, and in clinical states in which there is sodium retention with edema. In patients with diminished renal function, administration of solutions containing sodium ions may result in sodium retention. Infusion of isotonic (0.9%) sodium chloride during or immediately after surgery may result in excessive sodium retention. Use the patient's circulatory system status as a guide.

Excessive administration of potassium-free dextrose solutions may result in significant hypokalemia. Serum potassium levels should be maintained and potassium supplemented as required.

Solutions containing dextrose and low electrolyte concentrations should not be administered simultaneously with blood through the same infusion set because of the possibility of pseudoagglutination or hemolysis.

PRECAUTIONS

General

These solutions should be used with care in patients with hypervolemia, renal insufficiency, urinary tract obstruction, or impending or frank cardiac decompensation. Extraordinary electrolyte losses such as may occur during protracted nasogastric suction, vomiting, diarrhea or gastrointestinal fistula drainage may necessitate additional electrolyte supplementation.

Additional essential electrolytes, minerals and vitamins should be supplied as needed. Sodium-containing solutions should be administered with caution to patients receiving corticosteroids or corticotropin, or to other salt-retaining patients. Care should be exercised in administering solutions containing sodium to patients with renal or cardiovascular insufficiency, with or without congestive heart failure, particularly if they are postoperative or elderly.

Infusion of more than one liter of isotonic (0.9%) sodium chloride per day may supply more sodium and chloride than normally found in serum, and can exceed normal tolerance, resulting in hypernatremia; this may also cause a loss of bicarbonate ions, resulting in an acidifying effect.

Solutions containing dextrose should be used with caution in patients with overt or known subclinical diabetes mellitus, or carbohydrate intolerance for any reason. Hypokalemia may develop during parenteral administration of hypertonic dextrose solutions. Sufficient amounts of potassium should be added to dextrose solutions administered to fasting patients with good renal function, especially those on digitalis therapy.

To minimize the risk of possible incompatibilities arising from mixing any of these solutions with other additives that may be prescribed, the final infusate should be inspected for cloudiness or precipitation immediately after mixing, prior to administration and periodically during administration.

Do not use plastic containers in series connection.

If administration is controlled by a pumping device, care must be taken to discontinue pumping action before the container runs dry or air embolism may result. If administration is not controlled by a pumping device, refrain from applying excessive pressure (>300mmHg) causing distortion to the container such as wringing or twisting. Such handling could result in breakage of the container.

These solutions are intended for intravenous administration using sterile equipment. It is recommended that intravenous administration apparatus be replaced at least once every 24 hours.

Use only if solution is clear and container and seals are intact.

Laboratory Tests

Clinical evaluation and periodic laboratory determinations are necessary to monitor changes in fluid balance, electrolyte concentrations, and acid-base balance during prolonged parenteral therapy or whenever the condition of the patient warrants such evaluation. Significant deviations from normal concentrations may require tailoring of the electrolyte pattern, in these or alternative solutions.

Carcinogenesis, Mutagenesis, Impairment of Fertility

Studies with Dextrose and Sodium Chloride Injections USP have not been performed to evaluate carcinogenic potential, mutagenic potential, or effects on fertility.

Pregnancy

Teratogenic Effects

Animal reproduction studies have not been conducted with Dextrose and Sodium Chloride Injections USP. It is also not known whether Dextrose and Sodium Chloride Injections USP can cause fetal harm when administered to a pregnant woman or can affect reproduction capacity. Dextrose and Sodium Chloride Injections USP should be given to a pregnant woman only if clearly needed.

Labor and Delivery

The effects of Dextrose and Sodium Chloride Injections USP on the duration of labor or delivery, on the possibility that forceps delivery or other intervention or resuscitation of the newborn will be necessary, and on the later growth, development, and functional maturation of the child are unknown.

As reported in the literature, sodium and dextrose containing solutions have been administered during labor and delivery. Caution should be exercised, and the fluid balance, glucose and electrolyte concentrations, and acid-base balance, of both mother and fetus should be evaluated periodically or whenever warranted by the condition of the patient or fetus.

Nursing Mothers

It is not known whether this drug is excreted in human milk. Because many drugs are excreted in human milk, caution should be exercised when Dextrose and Sodium Chloride Injections USP are administered to a nursing woman.

Pediatric Use

Safety and effectiveness of Dextrose and Sodium Chloride Injections USP in pediatric patients have not been established by adequate and well-controlled studies.

Dextrose is safe and effective for the stated indications in pediatric patients (see INDICATIONS AND USAGE). As reported in the literature, the dosage selection and constant infusion rate of intravenous dextrose must be selected with caution in pediatric patients, particularly neonates and low birth weight infants, because of the increased risk of hyperglycemia/hypoglycemia. Frequent monitoring of serum glucose concentrations is required when dextrose is prescribed to pediatric patients, particularly neonates and low birth weight infants.

In neonates or in very small infants even small volumes of fluid may affect fluid and electrolyte balance. Care must be exercised in treatment of neonates, especially pre-term neonates, whose renal function may be immature and whose ability to excrete fluid and solute loads may be limited. Fluid intake, urine output, and serum electrolytes should be monitored closely. See WARNINGS and DOSAGE AND ADMINISTRATION.

Geriatric Use

Clinical studies of Dextrose and Sodium Chloride Injections USP did not include sufficient numbers of subjects aged 65 and over to determine whether they respond differently from younger subjects. Other reported clinical experience has not identified differences in responses between elderly and younger patients.

In general, dose selection for an elderly patient should be cautious, usually starting at the low end of the dosing range, reflecting the greater frequency of decreased hepatic, renal, or cardiac function, and of concomitant disease or other drug therapy.

These drugs are known to be substantially excreted by the kidney, and the risk of toxic reactions to these drugs may be greater in patients with impaired renal function. Because elderly patients are more likely to have decreased renal function, care should be taken in dose selection, and it may be useful to monitor renal function.

See WARNINGS.

ADVERSE REACTIONS

Reactions which may occur because of the solution or the technique of administration include febrile response, infection at the site of injection, venous thrombosis or phlebitis extending from the site of injection, extravasation and hypervolemia.

Too rapid infusion of hypertonic solutions may cause local pain and venous irritation. Rate of administration should be adjusted according to tolerance. Use of the largest peripheral vein and a small bore needle is recommended. (See DOSAGE AND ADMINISTRATION.)

Symptoms may result from an excess or deficit of one or more of the ions present in the solution; therefore, frequent monitoring of electrolyte levels is essential.

Hypernatremia may be associated with edema and exacerbation of congestive heart failure due to the retention of water, resulting in an expanded extracellular fluid volume. If infused in large amounts, chloride ions may cause a loss of bicarbonate ions, resulting in an acidifying effect.

The physician should also be alert to the possibility of adverse reactions to drug additives diluted and administered from the plastic container. Prescribing information for drug additives to be administered in this manner should be consulted.

If an adverse reaction does occur, discontinue the infusion, evaluate the patient, institute appropriate therapeutic countermeasures, and save the remainder of the fluid for examination if deemed necessary.

OVERDOSAGE

In the event of a fluid or solute overload during parenteral therapy, reevaluate the patient's condition and institute appropriate corrective treatment.

DOSAGE AND ADMINISTRATION

These solutions are for intravenous use only.

Dosage is to be directed by a physician and is dependent upon age, weight, clinical condition of the patient and laboratory determinations. Frequent laboratory determinations and clinical evaluation are essential to monitor changes in blood glucose and electrolyte concentrations, and fluid and electrolyte balance during prolonged parenteral therapy.

When a hypertonic solution is to be administered peripherally, it should be slowly infused through a small bore needle, placed well within the lumen of a large vein to minimize venous irritation. Carefully avoid infiltration.

In the average adult, daily requirements of sodium and chloride are met by the infusion of one liter of fluid containing 0.9% sodium chloride (154 mEq each of sodium and chloride).

Fluid administration should be based on calculated maintenance or replacement fluid requirements for each patient.

Some additives may be incompatible. Consult with pharmacist. When introducing additives, use aseptic techniques. Mix thoroughly. Do not store.

Parenteral drug products should be inspected visually for particulate matter and discoloration prior to administration, whenever solution and container permit.

Pediatric Use

There is no specific pediatric dose. The dose is dependent on weight, clinical condition, and laboratory results. See WARNINGS and PRECAUTIONS.

HOW SUPPLIED

Dextrose and Sodium Chloride Injections USP are supplied sterile and nonpyrogenic in EXCEL® Containers. The 1000 mL containers are packaged 12 per case; the 500 mL and 250 mL containers are packaged 24 per case.

Canada DIN | NDC | REF | Size
3.3% Dextrose and 0.30% Sodium Chloride Injection USP
01927981 | 0264-7608-00 | L6080-00 | 1000 mL
 | 0264-7608-10 | L6081-00 | 500 mL
5% Dextrose and 0.9% Sodium Chloride Injection USP
01924435 | 0264-7610-00 | L6100 | 1000 mL
 | 0264-7610-10 | L6101 | 500 mL
5% Dextrose and 0.45% Sodium Chloride Injection USP
01927531 | 0264-7612-00 | L6120 | 1000 mL
 | 0264-7612-10 | L6121 | 500 mL
 | 0264-7612-20 | L6122 | 250 mL
5% Dextrose and 0.33% Sodium Chloride Injection USP
 | 0264-7614-00 | L6140 | 1000 mL
 | 0264-7614-10 | L6141 | 500 mL
5% Dextrose and 0.20% Sodium Chloride Injection USP
01927558 | 0264-7616-00 | L6160 | 1000 mL
 | 0264-7616-10 | L6161 | 500 mL
 | 0264-7616-20 | L6162 | 250 mL
10% Dextrose and 0.45% Sodium Chloride Injection USP
 | 0264-7622-00 | L6220 | 1000 mL
10% Dextrose and 0.20% Sodium Chloride Injection USP
 | 0264-7623-20 | L6232 | 250 mL

STORAGE AND HANDLING

Exposure of pharmaceutical products to heat should be minimized. Avoid excessive heat. Protect from freezing. It is recommended that the product be stored at room temperature (25°C); however, brief exposure up to 40°C does not adversely affect the product.

Rx only

Revised: November 2018
EXCEL is a registered trademark of B. Braun Medical Inc.

Directions for Use of EXCEL® Container

Caution: Do not use plastic containers in series connection.

To Open

Tear overwrap down at notch and remove solution container. Check for minute leaks by squeezing solution container firmly. If leaks are found, discard solution as sterility may be impaired. If supplemental medication is desired, follow directions below before preparing for administration.

NOTE: Before use, perform the following checks:

Inspect each container. Read the label. Ensure solution is the one ordered and is within the expiration date.

Invert container and carefully inspect the solution in good light for cloudiness, haze, or particulate matter. Any container which is suspect should not be used.

Use only if solution is clear and container and seals are intact.

Preparation for Administration

1. Remove plastic protector from sterile set port at bottom of container.
2. Attach administration set. Refer to complete directions accompanying set.

To Add Medication

Warning: Some additives may be incompatible.

To Add Medication Before Solution Administration

1. Prepare medication site.
2. Using syringe with 18 – 22 Ga. needle, puncture medication port and inner diaphragm and inject.
3. Squeeze and tap ports while ports are upright and mix solution and medication thoroughly.

To Add Medication During Solution Administration

1. Close clamp on the set.
2. Prepare medication site.
3. Using syringe with 18 – 22 Ga. needle of appropriate length (at least 5/8 inch), puncture
resealable medication port and inner diaphragm and inject.
4. Remove container from IV pole and/or turn to an upright position.
5. Evacuate both ports by tapping and squeezing them while container is in the upright position.
6. Mix solution and medication thoroughly.
7. Return container to in use position and continue administration.

B. Braun Medical Inc.
Bethlehem, PA 18018-3524 USA
1-800-227-2862

In Canada, distributed by:
B. Braun of Canada, Ltd.
Scarborough, Ontario M1H 2W4

Y36-002-948

LD-197-4

PRINCIPAL DISPLAY PANEL - 1000 mL Container Label

3.3% Dextrose and
0.30% Sodium Chloride
Injection USP
REF L6080-00
NDC 0264-7608-00
DIN 01927981

1000 mL
EXCEL® CONTAINER
Each 100 mL contains: Hydrous Dextrose USP 3.3 g;
Sodium Chloride USP 0.3 g; Water for Injection USP qs

pH: 4.5 (3.5-6.5); Calc. Osmolarity: 270 mOsmol/liter

Electrolytes (mEq/liter): Na^+ 51; Cl^– 51

Sterile, nonpyrogenic. Single dose container. Do not use in
series connection. For intravenous use only. Use only if
solution is clear and container and seals are intact.

WARNINGS: Do Not Administer Simultaneously With
Blood. Some additives may be incompatible. Consult
with pharmacist. When introducing additives, use aseptic
techniques. Mix thoroughly. Do not store.

Recommended Storage: Room temperature (25°C). Avoid
excessive heat. Protect from freezing. See Package Insert.

Do not remove overwrap until ready for use. After removing the
overwrap, check for minute leaks by squeezing container firmly. If
leaks are found, discard solution as sterility may be impaired.

Not made with natural rubber latex, PVC or DEHP.

Rx only

EXCEL is a registered trademark of B. Braun Medical Inc.

B. Braun Medical Inc.
Bethlehem, PA 18018-3524 USA
1-800-227-2862
In Canada, distributed by:
B. Braun of Canada, Ltd.
Scarborough, Ontario M1H 2W4

Y94-003-252
LD-183-3

EXP
LOT

PRINCIPAL DISPLAY PANEL - 500 mL Container Label

3.3% Dextrose and
0.30% Sodium Chloride
Injection USP

REF L6081-00
NDC 0264-7608-10
DIN 01927981
500 mL
EXCEL® CONTAINER

Each 100 mL contains: Hydrous Dextrose USP 3.3 g; Sodium Chloride USP 0.3 g;
Water for Injection USP qs

pH: 4.5 (3.5-6.5); Calc. Osmolarity: 270 mOsmol/liter

Electrolytes (mEq/liter): Na^+ 51; Cl^– 51

Sterile, nonpyrogenic. Single dose container. Do not use in series connection. For
intravenous use only. Use only if solution is clear and container and seals are intact.

WARNINGS: Do Not Administer Simultaneously With Blood. Some additives may be
incompatible. Consult with pharmacist. When introducing additives, use aseptic
techniques. Mix thoroughly. Do not store.

Recommended Storage: Room temperature (25°C). Avoid excessive heat. Protect from
freezing. See Package Insert.

Do not remove overwrap until ready for use. After removing the overwrap, check for minute
leaks by squeezing container firmly. If leaks are found, discard solution as sterility may
be impaired.

Not made with natural rubber latex, PVC or DEHP.

Rx only

EXCEL is a registered trademark of B. Braun Medical Inc.

B. Braun Medical Inc.
Bethlehem, PA 18018-3524 USA
1-800-227-2862
In Canada, distributed by:
B. Braun of Canada, Ltd.
Scarborough, Ontario M1H 2W4

Y94-003-246
LD-184-3

EXP
LOT

L6081-00

PRINCIPAL DISPLAY PANEL - 1000 mL Container Label

5% Dextrose and
0.9% Sodium Chloride
Injection USP

REF L6100
NDC 0264-7610-00
DIN 01924435
HK 22608

1000 mL
EXCEL® CONTAINER

Each 100 mL contains: Hydrous Dextrose USP 5 g;
Sodium Chloride USP 0.9 g; Water for Injection USP qs

pH: 4.4 (3.5-6.5); Calc. Osmolarity: 560 mOsmol/liter,
hypertonic

Electrolytes (mEq/liter): Na^+ 154; Cl^– 154

Sterile, nonpyrogenic. Single dose container. Do not use in
series connection. For intravenous use only. Use only if
solution is clear and container and seals are intact.

WARNINGS: Some additives may be incompatible. Consult
with pharmacist. When introducing additives, use aseptic
techniques. Mix thoroughly. Do not store.

Recommended Storage: Room temperature (25°C). Avoid
excessive heat. Protect from freezing. See Package Insert.

Do not remove overwrap until ready for use. After removing the
overwrap, check for minute leaks by squeezing container firmly. If
leaks are found, discard solution as sterility may be impaired.

Not made with natural rubber latex, PVC or DEHP.

Rx only

EXCEL is a registered trademark of B. Braun Medical Inc.

B. Braun Medical Inc.
Bethlehem, PA 18018-3524 USA
1-800-227-2862

In Canada, distributed by:
B. Braun of Canada, Ltd.
Scarborough, Ontario M1H 2W4

Y94-003-253
LD-177-3

EXP
LOT

PRINCIPAL DISPLAY PANEL - 500 mL Container Label

5% Dextrose and
0.9% Sodium Chloride
Injection USP

REF L6101
NDC 0264-7610-10
DIN 01924435
HK 22608

500 mL
EXCEL® CONTAINER

Each 100 mL contains: Hydrous Dextrose USP 5 g; Sodium Chloride USP 0.9 g;
Water for Injection USP qs

pH: 4.4 (3.5-6.5); Calc. Osmolarity: 560 mOsmol/liter, hypertonic

Electrolytes (mEq/liter): Na^+ 154; Cl^– 154

Sterile, nonpyrogenic. Single dose container. Do not use in series connection. For
intravenous use only. Use only if solution is clear and container and seals are
intact.

WARNINGS: Some additives may be incompatible. Consult with pharmacist. When
introducing additives, use aseptic techniques. Mix thoroughly. Do not store.

Recommended Storage: Room temperature (25°C). Avoid excessive heat. Protect
from freezing. See Package Insert.

Do not remove overwrap until ready for use. After removing the overwrap, check for minute
leaks by squeezing container firmly. If leaks are found, discard solution as sterility
may be impaired.

Not made with natural rubber latex, PVC or DEHP.

Rx only

EXCEL is a registered trademark of B. Braun Medical Inc.

B. Braun Medical Inc.
Bethlehem, PA 18018-3524 USA
1-800-227-2862

In Canada, distributed by:
B. Braun of Canada, Ltd.
Scarborough, Ontario M1H 2W4

Y94-003-247
LD-176-3

EXP
LOT

L6101

PRINCIPAL DISPLAY PANEL - 1000 mL Container Label

5% Dextrose and
0.45% Sodium Chloride
Injection USP

REF L6120
NDC 0264-7612-00
DIN 01927531
HK 22607

1000 mL
EXCEL® CONTAINER

Each 100 mL contains: Hydrous Dextrose USP 5 g;
Sodium Chloride USP 0.45 g; Water for Injection USP qs

pH: 4.4 (3.5-6.5); Calc. Osmolarity: 405 mOsmol/liter,
hypertonic

Electrolytes (mEq/liter): Na^+ 77; Cl^– 77

Sterile, nonpyrogenic. Single dose container. Do not use in
series connection. For intravenous use only. Use only if
solution is clear and container and seals are intact.

WARNINGS: Some additives may be incompatible. Consult
with pharmacist. When introducing additives, use aseptic
techniques. Mix thoroughly. Do not store.

Recommended Storage: Room temperature (25°C). Avoid
excessive heat. Protect from freezing. See Package Insert.

Do not remove overwrap until ready for use. After removing the
overwrap, check for minute leaks by squeezing container firmly. If
leaks are found, discard solution as sterility may be impaired.

Not made with natural rubber latex, PVC or DEHP.

Rx only
EXCEL is a registered trademark of B. Braun Medical Inc.

B. Braun Medical Inc.
Bethlehem, PA 18018-3524 USA
1-800-227-2862

In Canada, distributed by:
B. Braun of Canada, Ltd.
Scarborough, Ontario M1H 2W4

Y94-003-254
LD-108-3

EXP
LOT

PRINCIPAL DISPLAY PANEL - 500 mL Container Label

5% Dextrose and
0.45% Sodium Chloride
Injection USP

REF L6121
NDC 0264-7612-10
DIN 01927531
HK 22607

500 mL
EXCEL® CONTAINER

Each 100 mL contains: Hydrous Dextrose USP 5 g; Sodium Chloride USP 0.45 g;
Water for Injection USP qs

pH: 4.4 (3.5-6.5); Calc. Osmolarity: 405 mOsmol/liter, hypertonic

Electrolytes (mEq/liter): Na^+ 77; Cl^– 77

Sterile, nonpyrogenic. Single dose container. Do not use in series connection. For
intravenous use only. Use only if solution is clear and container and seals are
intact.

WARNINGS: Some additives may be incompatible. Consult with pharmacist. When
introducing additives, use aseptic techniques. Mix thoroughly. Do not store.

Recommended Storage: Room temperature (25°C). Avoid excessive heat. Protect
from freezing. See Package Insert.

Do not remove overwrap until ready for use. After removing the overwrap, check for minute
leaks by squeezing container firmly. If leaks are found, discard solution as sterility
may be impaired.

Not made with natural rubber latex, PVC or DEHP.

Rx only

EXCEL is a registered trademark of B. Braun Medical Inc.

B. Braun Medical Inc.
Bethlehem, PA 18018-3524 USA
1-800-227-2862

In Canada, distributed by:
B. Braun of Canada, Ltd.
Scarborough, Ontario M1H 2W4

Y94-003-248
LD-113-3

EXP
LOT

L6121

PRINCIPAL DISPLAY PANEL - 250 mL Container Label

5% Dextrose and
0.45% Sodium Chloride
Injection USP

REF L6122
NDC 0264-7612-20
DIN 01927531
HK 22607
250 mL
EXCEL® CONTAINER
Each 100 mL contains: Hydrous Dextrose USP 5 g; Sodium
Chloride USP 0.45 g; Water for Injection USP qs

pH: 4.4 (3.5-6.5); Calc. Osmolarity: 405 mOsmol/liter,
hypertonic

Electrolytes (mEq/liter): Na^+ 77; Cl^– 77

Sterile, nonpyrogenic. Single dose container. Do not use in series
connection. For intravenous use only. Use only if solution is clear and
container and seals are intact.

WARNINGS: Some additives may be incompatible. Consult with
pharmacist. When introducing additives, use aseptic techniques.
Mix thoroughly. Do not store.

Recommended Storage: Room temperature (25°C). Avoid excessive
heat. Protect from freezing. See Package Insert.

Do not remove overwrap until ready for use. After removing the overwrap,
check for minute leaks by squeezing container firmly. If leaks are found,
discard solution as sterility may be impaired.

Not made with natural rubber latex, PVC or DEHP.

Rx only
EXCEL is a registered trademark of B. Braun Medical Inc.

B. Braun Medical Inc.
Bethlehem, PA 18018-3524 USA
1-800-227-2862
In Canada, distributed by:
B. Braun of Canada, Ltd.
Scarborough, Ontario M1H 2W4

Y94-003-245
LD-114-3

EXP
LOT

L6122

PRINCIPAL DISPLAY PANEL - 1000 mL Container Label

5% Dextrose and
0.33% Sodium Chloride
Injection USP

REF L6140
NDC 0264-7614-00

1000 mL
EXCEL® CONTAINER

Each 100 mL contains: Hydrous Dextrose USP 5 g;
Sodium Chloride USP 0.33 g; Water for Injection USP qs

pH: 4.4 (3.5-6.5); Calc. Osmolarity: 365 mOsmol/liter,
hypertonic

Electrolytes (mEq/liter): Na^+ 56; Cl^– 56

Sterile, nonpyrogenic. Single dose container. Do not use in
series connection. For intravenous use only. Use only if
solution is clear and container and seals are intact.

WARNINGS: Do Not Administer Simultaneously With Blood.
Some additives may be incompatible. Consult with
pharmacist. When introducing additives, use aseptic
techniques. Mix thoroughly. Do not store.

Recommended Storage: Room temperature (25°C). Avoid
excessive heat. Protect from freezing. See Package Insert.

Do not remove overwrap until ready for use. After removing the
overwrap, check for minute leaks by squeezing container firmly. If
leaks are found, discard solution as sterility may be impaired.

Not made with natural rubber latex, PVC or DEHP.

Rx only

EXCEL is a registered trademark of B. Braun Medical Inc.

B. Braun Medical Inc.
Bethlehem, PA 18018-3524 USA
1-800-227-2862

Y94-003-255
LD-115-3

EXP
LOT

PRINCIPAL DISPLAY PANEL - 500 mL Container Label

5% Dextrose and
0.33% Sodium Chloride
Injection USP

REF L6141
NDC 0264-7614-10

500 mL
EXCEL® CONTAINER

Each 100 mL contains: Hydrous Dextrose USP 5 g; Sodium Chloride USP 0.33 g;
Water for Injection USP qs

pH: 4.4 (3.5-6.5); Calc. Osmolarity: 365 mOsmol/liter, hypertonic

Electrolytes (mEq/liter): Na^+ 56; Cl^– 56

Sterile, nonpyrogenic. Single dose container. Do not use in series connection. For
intravenous use only. Use only if solution is clear and container and seals are intact.

WARNINGS: Do Not Administer Simultaneously With Blood. Some additives may be
incompatible. Consult with pharmacist. When introducing additives, use aseptic
techniques. Mix thoroughly. Do not store.

Recommended Storage: Room temperature (25°C). Avoid excessive heat. Protect from
freezing. See Package Insert.

Do not remove overwrap until ready for use. After removing the overwrap, check for
minute leaks by squeezing container firmly. If leaks are found, discard solution as
sterility may be impaired.

Not made with natural rubber latex, PVC or DEHP.

Rx only

EXCEL is a registered trademark of B. Braun Medical Inc.

B. Braun Medical Inc.
Bethlehem, PA 18018-3524 USA
1-800-227-2862
Y94-003-249
LD-174-3

EXP
LOT

L6141

PRINCIPAL DISPLAY PANEL - 1000 mL Container Label

5% Dextrose and
0.20% Sodium Chloride
Injection USP

REF L6160
NDC 0264-7616-00
DIN 01927558
HK 22606

1000 mL
EXCEL® CONTAINER

Each 100 mL contains: Hydrous Dextrose USP 5 g;
Sodium Chloride USP 0.2 g; Water for Injection USP qs

pH: 4.4 (3.5-6.5); Calc. Osmolarity: 320 mOsmol/liter

Electrolytes (mEq/liter): Na^+ 34 ; Cl^– 34

Sterile, nonpyrogenic. Single dose container. Do not use in
series connection. For intravenous use only. Use only if
solution is clear and container and seals are intact.

WARNINGS: Do Not Administer Simultaneously With Blood.
Some additives may be incompatible. Consult with
pharmacist. When introducing additives, use aseptic
techniques. Mix thoroughly. Do not store.

Recommended Storage: Room temperature (25°C). Avoid
excessive heat. Protect from freezing. See Package Insert.

Do not remove overwrap until ready for use. After removing the
overwrap, check for minute leaks by squeezing container firmly. If
leaks are found, discard solution as sterility may be impaired.

Not made with natural rubber latex, PVC or DEHP.

Rx only

EXCEL is a registered trademark of B. Braun Medical Inc.

B. Braun Medical Inc.
Bethlehem, PA 18018-3524 USA
1-800-227-2862

In Canada, distributed by:
B. Braun of Canada, Ltd.
Scarborough, Ontario M1H 2W4

Y94-003-256
LD-172-3

EXP
LOT

PRINCIPAL DISPLAY PANEL - 500 mL Container Label

5% Dextrose and
0.20% Sodium Chloride
Injection USP

REF L6161
NDC 0264-7616-10
DIN 01927558
HK 22606

500 mL
EXCEL® CONTAINER

Each 100 mL contains: Hydrous Dextrose USP 5 g; Sodium Chloride USP 0.2 g;
Water for Injection USP qs

pH: 4.4 (3.5-6.5); Calc. Osmolarity: 320 mOsmol/liter

Electrolytes (mEq/liter): Na^+ 34; Cl^– 34

Sterile, nonpyrogenic. Single dose container. Do not use in series connection. For
intravenous use only. Use only if solution is clear and container and seals are intact.

WARNINGS: Do Not Administer Simultaneously With Blood. Some additives may be
incompatible. Consult with pharmacist. When introducing additives, use aseptic
techniques. Mix thoroughly. Do not store.

Recommended Storage: Room temperature (25°C). Avoid excessive heat. Protect from
freezing. See Package Insert.

Do not remove overwrap until ready for use. After removing the overwrap, check for minute
leaks by squeezing container firmly. If leaks are found, discard solution as sterility may
be impaired.

Not made with natural rubber latex, PVC or DEHP.

Rx only

EXCEL is a registered trademark of B. Braun Medical Inc.

B. Braun Medical Inc.
Bethlehem, PA 18018-3524 USA
1-800-227-2862

In Canada, distributed by:
B. Braun of Canada, Ltd.
Scarborough, Ontario M1H 2W4

Y94-003-250
LD-112-3

EXP
LOT

L6161

PRINCIPAL DISPLAY PANEL - 250 mL Container Label

5% Dextrose and
0.20% Sodium Chloride
Injection USP

REF L6162
NDC 0264-7616-20
DIN 01927558
HK 22606

250 mL
EXCEL® CONTAINER

Each 100 mL contains: Hydrous Dextrose USP 5 g; Sodium
Chloride USP 0.2 g; Water for Injection USP qs

pH: 4.4 (3.5-6.5); Calc. Osmolarity: 320 mOsmol/liter
Electrolytes (mEq/liter): Na^+ 34; Cl^– 34

Sterile, nonpyrogenic. Single dose container. Do not use in series
connection. For intravenous use only. Use only if solution is clear and
container and seals are intact.

WARNINGS: Do Not Administer Simultaneously With Blood. Some
additives may be incompatible. Consult with pharmacist. When
introducing additives, use aseptic techniques. Mix thoroughly.
Do not store.

Recommended Storage: Room temperature (25°C). Avoid excessive
heat. Protect from freezing. See Package Insert.

Do not remove overwrap until ready for use. After removing the overwrap,
check for minute leaks by squeezing container firmly. If leaks are found,
discard solution as sterility may be impaired.

Not made with natural rubber latex, PVC or DEHP.

Rx only

EXCEL is a registered trademark of B. Braun Medical Inc.

B. Braun Medical Inc.
Bethlehem, PA 18018-3524 USA
1-800-227-2862

In Canada, distributed by:
B. Braun of Canada, Ltd.
Scarborough, Ontario M1H 2W4

Y94-003-258
LD-171-3

EXP
LOT

L6162

PRINCIPAL DISPLAY PANEL - 1000 mL Container Label

10% Dextrose and
0.45% Sodium Chloride
Injection USP

REF L6220
NDC 0264-7622-00

1000 mL
EXCEL® CONTAINER

Each 100 mL contains: Hydrous Dextrose USP 10 g;
Sodium Chloride USP 0.45 g; Water for Injection USP qs

pH: 4.3 (3.5-6.5); Calc. Osmolarity: 660 mOsmol/liter,
hypertonic

Electrolytes (mEq/liter): Na^+ 77; Cl^– 77

Sterile, nonpyrogenic. Single dose container. Do not use in
series connection. For intravenous use only. Use only if
solution is clear and container and seals are intact.

WARNINGS: Some additives may be incompatible. Consult
with pharmacist. When introducing additives, use aseptic
techniques. Mix thoroughly. Do not store.

Recommended Storage: Room temperature (25°C). Avoid
excessive heat. Protect from freezing. See Package Insert.

Do not remove overwrap until ready for use. After removing the
overwrap, check for minute leaks by squeezing container firmly. If
leaks are found, discard solution as sterility may be impaired.

Not made with natural rubber latex, PVC or DEHP.

Rx only

EXCEL is a registered trademark of B. Braun Medical Inc.

B. Braun Medical Inc.
Bethlehem, PA 18018-3524 USA
1-800-227-2862

Y94-003-257
LD-170-3

EXP
LOT

PRINCIPAL DISPLAY PANEL - 250 mL Container Label

10% Dextrose and
0.20% Sodium Chloride
Injection USP
REF L6232
NDC 0264-7623-20
250 mL
EXCEL® CONTAINER

Each 100 mL contains: Hydrous Dextrose USP 10 g;
Sodium Chloride USP 0.2 g; Water for Injection USP qs

pH: 4.3 (3.5-6.5); Calc. Osmolarity: 575 mOsmol/liter,
hypertonic

Electrolytes (mEq/liter): Na^+ 34; Cl^– 34

Sterile, nonpyrogenic. Single dose container. Do not use in series
connection. For intravenous use only. Use only if solution is
clear and container and seals are intact.

WARNINGS: Do Not Administer Simultaneously With Blood.
Some additives may be incompatible. Consult with pharmacist.
When introducing additives, use aseptic techniques. Mix
thoroughly. Do not store.

Recommended Storage: Room temperature (25°C). Avoid
excessive heat. Protect from freezing. See Package Insert.

Do not remove overwrap until ready for use. After removing the overwrap,
check for minute leaks by squeezing container firmly. If leaks are found,
discard solution as sterility may be impaired.

Not made with natural rubber latex, PVC or DEHP.

Rx only

EXCEL is a registered trademark of B. Braun Medical Inc.

B. Braun Medical Inc.
Bethlehem, PA 18018-3524 USA
1-800-227-2862

Y94-003-259
LD-169-4

EXP
LOT

L6232